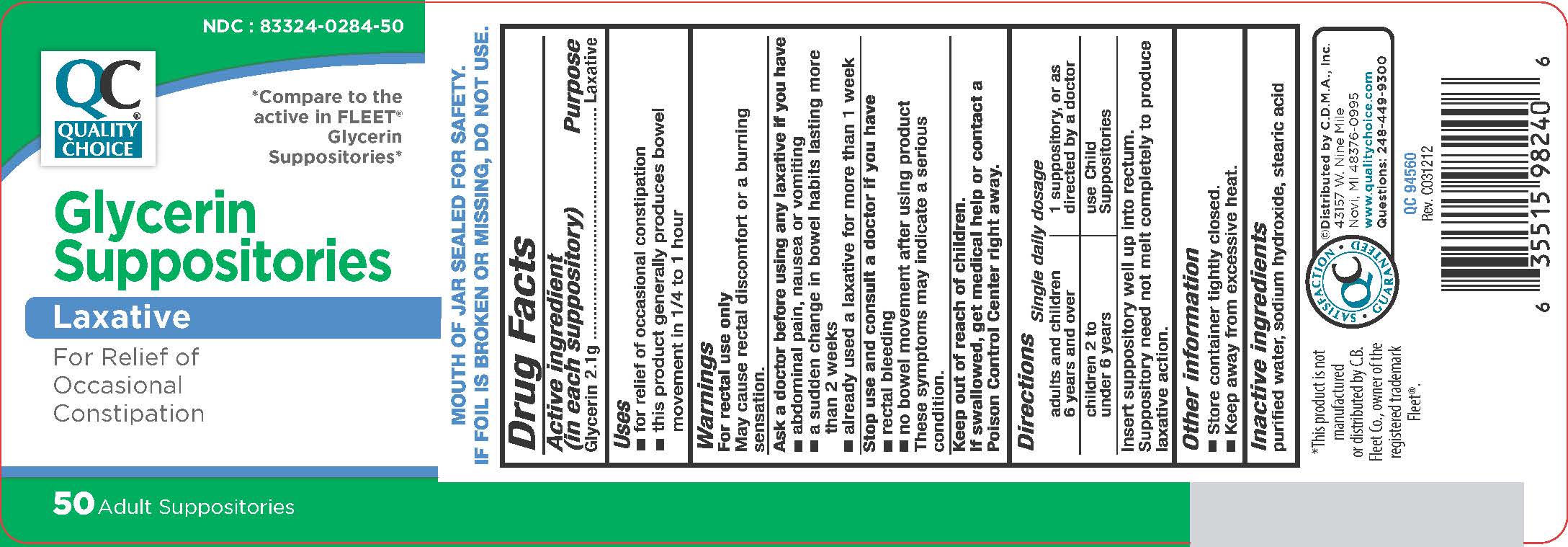 DRUG LABEL: Glycerin								
NDC: 83324-284 | Form: SUPPOSITORY
Manufacturer: Chain Drug Marketing Association Inc.
Category: otc | Type: HUMAN OTC DRUG LABEL
Date: 20251029

ACTIVE INGREDIENTS: GLYCERIN 2.1 g/1 1
INACTIVE INGREDIENTS: WATER; SODIUM HYDROXIDE; STEARIC ACID

Quality Choice Glycerin Supp.

Active ingredient (in each suppository)

Glycerin 2.1 g

Purpose

Laxative

Uses

- for relief of occasional constipation
- this product generally produces a bowel movement in 1/4 to 1 hour

Warnings

For rectal use only

May cause rectal discomfort of burning sensation

Ask a Doctor before using any laxative if you have

- abdominal pain, nausea or vomiting
- a sudden change in bowel habits lasting more than 2 weeks
- already used a laxative for more than 1 week

Stop use and consult a doctor if you have

- rectal bleeding
- no bowel movement after using this product

These symptoms may indicate a serious condition.

Keep out of reach of children.

If swallowed, get medical help or contact a Poison Control Center right away.

Directions

Single daily dosage

adults and children 6 years and over 1 suppository, or as directed by a doctor

children 2 to under 6 years use Child Suppositories

Insert suppository well up into rectum.

Suppository need not melt completely to produce laxative action.

Other information

- Store container tightly closed.
- Keep away from excessive heat.

Inactive ingredients

purified water, sodium hydroxide, stearic acid

Glycerin Suppositories, 50 count

The product package shown below represents a sample of that currently in use. Additional packaging may also be available.

Glycerin Suppositories, 50 count

Distributed by Quality Choice

Novi, MI 48376-0995

www.qualitychoice.com

QC_50ct.jpg